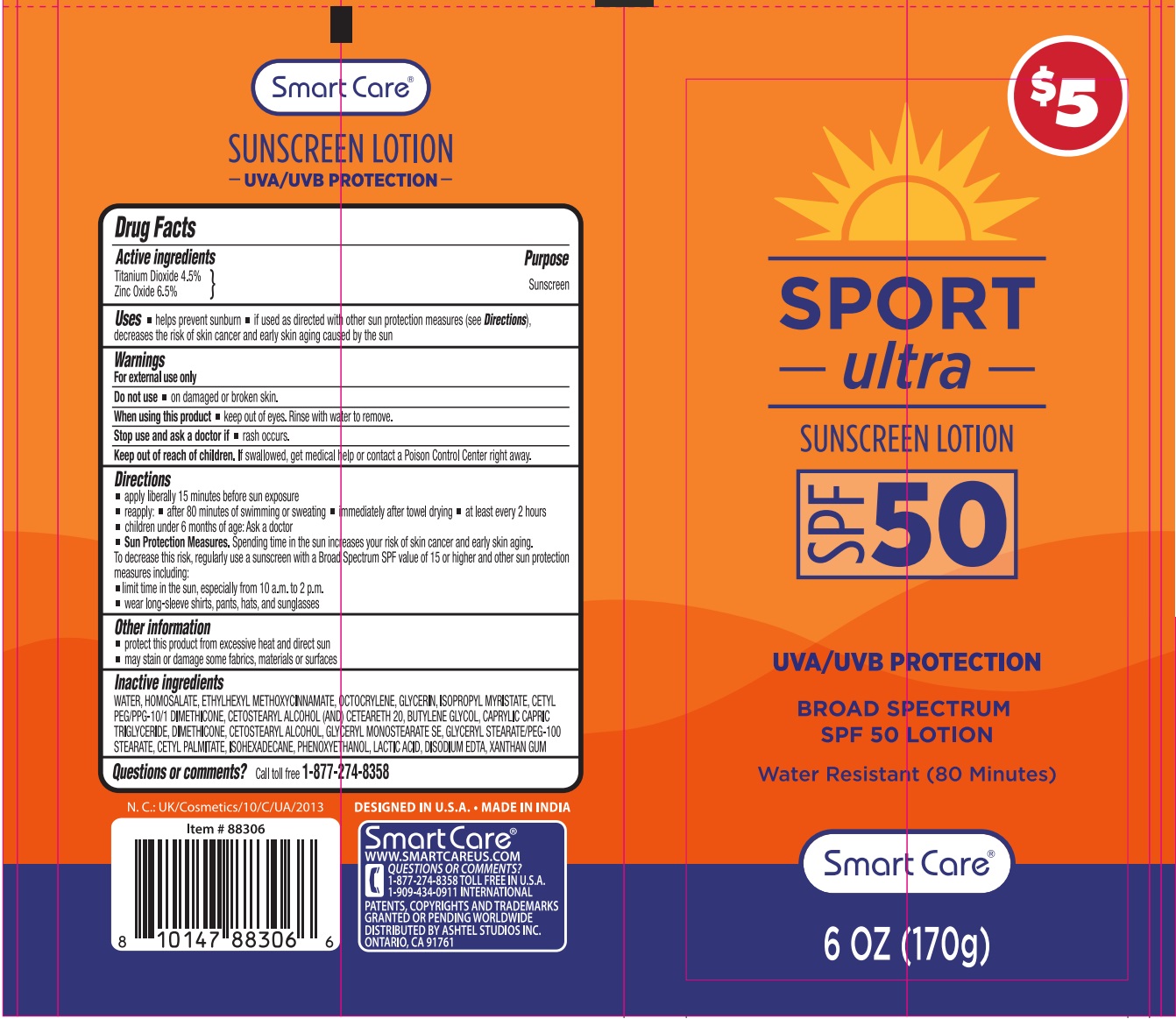 DRUG LABEL: Smart Care SPORT ultra SUNSCREEN SPF 50
NDC: 70108-116 | Form: LOTION
Manufacturer: Ashtel Studios Inc.
Category: otc | Type: HUMAN OTC DRUG LABEL
Date: 20250211

ACTIVE INGREDIENTS: TITANIUM DIOXIDE 4.5 g/100 g; ZINC OXIDE 6.5 g/100 g
INACTIVE INGREDIENTS: WATER; HOMOSALATE; OCTINOXATE; OCTOCRYLENE; GLYCERIN; ISOPROPYL MYRISTATE; CETYL PEG/PPG-10/1 DIMETHICONE (HLB 2); CETOSTEARYL ALCOHOL; POLYOXYL 20 CETOSTEARYL ETHER; BUTYLENE GLYCOL; MEDIUM-CHAIN TRIGLYCERIDES; DIMETHICONE, UNSPECIFIED; GLYCERYL STEARATE SE; GLYCERYL STEARATE/PEG-100 STEARATE; CETYL PALMITATE; ISOHEXADECANE; PHENOXYETHANOL; LACTIC ACID, UNSPECIFIED FORM; EDETATE DISODIUM; XANTHAN GUM

Smart Care® SPORT ultra SUNSCREEN LOTION

Active ingredients

Titanium Dioxide 4.5%
Zinc Oxide 6.5%

Purpose

Sunscreen

Uses

• helps prevent sunburn • if used as directed with other sun protection measures (see Directions), decreases the risk of skin cancer and early skin aging caused by the sun

Warnings

For external use only

Do not use • on damaged or broken skin.

When using this product • keep out of eyes. Rinse with water to remove.

Stop use and ask a doctor if • rash occurs.

Keep out of reach of children. If swallowed, get medical help or contact a Poison Control Center right away.

Directions

• apply liberally 15 minutes before sun exposure
• reapply: • after 80 minutes of swimming or sweating • immediately after towel drying • at least every 2 hours
• children under 6 months of age: Ask a doctor
• Sun Protection Measures. Spending time in the sun increases your risk of skin cancer and early skin aging. To decrease this risk, regularly use a sunscreen with a Broad Spectrum SPF value of 15 or higher and other sun protection measures including:
• limit time in the sun, especially from 10 a.m. to 2 p.m.
• wear long-sleeve shirts, pants, hats, and sunglasses

Other information

• protect this product from excessive heat and direct sun
• may stain or damage some fabrics, materials or surfaces

Inactive ingredients

WATER, HOMOSALATE, ETHYLHEXYL METHOXYCINNAMATE, OCTOCRYLENE, GLYCERIN, ISOPROPYL MYRISTATE, CETYL PEG/PPG-10/1 DIMETHICONE, CETOSTEARYL ALCOHOL (AND) CETEARETH 20, BUTYLENE GLYCOL, CAPRYLIC CAPRIC TRIGLYCERIDE, DIMETHICONE, CETOSTEARYL ALCOHOL, GLYCERYL MONOSTEARATE SE, GLYCERYL STEARATE/PEG-100 STEARATE, CETYL PALMITATE, ISOHEXADECANE, PHENOXYETHANOL, LACTIC ACID, DISODIUM EDTA, XANTHAN GUM

Questions or comments?

Call toll free 1-877-274-8358

UVA/UVB PROTECTION

BROAD SPECTRUM

Water Resistant (80 Minutes)

DESIGNED IN U.S.A. • MADE IN INDIA

WWW.SMARTCAREUS.COM
1-909-434-0911 INTERNATIONAL
PATENTS, COPYRIGHTS AND TRADEMARKS GRANTED OR PENDING WORLDWIDE
DISTRIBUTED BY ASHTEL STUDIOS INC.
ONTARIO, CA 91761